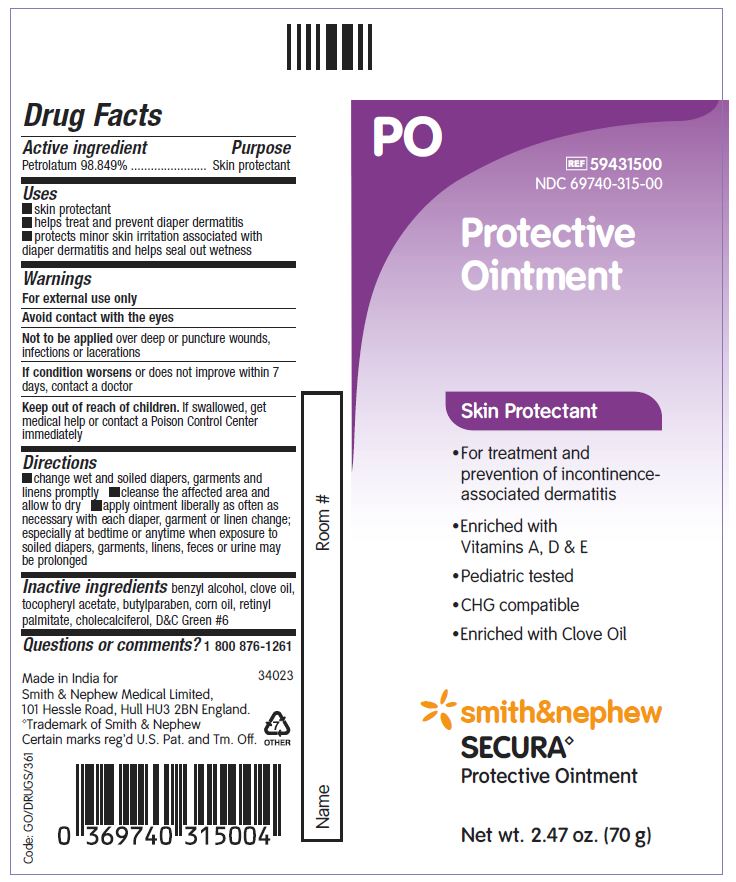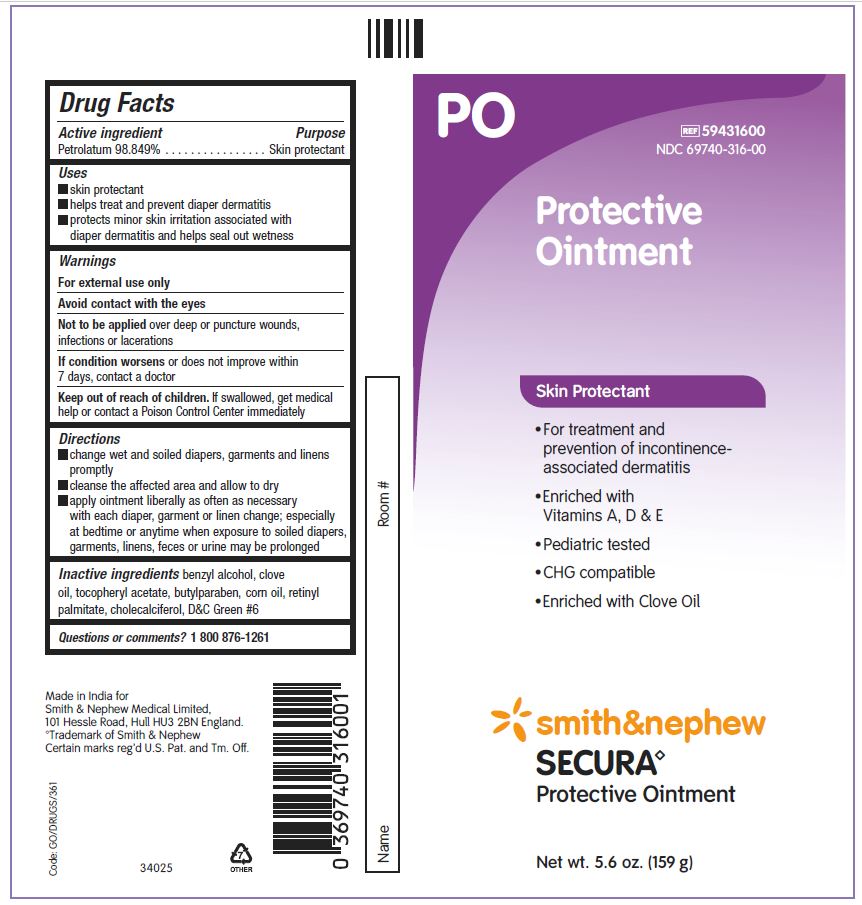 DRUG LABEL: Secura Protective
NDC: 69740-315 | Form: OINTMENT
Manufacturer: Smith & Nephew Medical Ltd
Category: otc | Type: HUMAN OTC DRUG LABEL
Date: 20240612

ACTIVE INGREDIENTS: PETROLATUM 988.49 mg/1 g
INACTIVE INGREDIENTS: BUTYLPARABEN; BENZYL ALCOHOL; CLOVE OIL; D&C GREEN NO. 6; ALPHA-TOCOPHEROL ACETATE; CHOLECALCIFEROL; VITAMIN A PALMITATE; CORN OIL

Secura Protective Ointment

ACTIVE INGREDIENTS

Petrolatum 98.849%

PURPOSE

Skin Protectant

USES

- Skin protectant
- Helps treat and prevent diaper dermatitis
- Protects minor skin irritation associated with diaper dermatitis and helps seal out wetness

WARNINGS

- For external use only
- Avoid contact with the eyes

- Not to be applied over deep or puncture wounds, infections or lacerations

- If condition worsensor does not improve within 7 days, contact a doctor

KEEP OUT OF REACH OF CHILDREN

If swallowed, get medical help or contact a Poison Control Center immediately.

DIRECTIONS

- change wet and soiled diapers, garments and linens promptly
- cleanse the affected area and allow to dry
- apply ointment liberally as often as necessary with each diaper, garment or linen change; especially at bedtime or anytime when exposure to soiled diapers, garments, linens, feces, or urine may be prolonged

INACTIVE INGREDIENTS

benzyl alcohol, clove oil, tocopheryl acetate, butylparaben, corn oil, retinyl palmitate, cholecalciferold, D&C Green #6

QUESTIONS OR COMMENTS?

1 800 876-1261

PACKAGE LABEL - PRINCIPAL DISPLAY PANEL - SECURA PROTECTIVE OINTMENT (70g)

#59431500

NDC-69740-315-00

Protective Ointment

Skin Protectant

- For treatment and prevention of incontinence-associated dermatitis
- Enriched with Vitamins A, D & E
- Pediatric tested
- CHG compatible
- Enriched with Clove Oil

Smith&Nephew

Secura

Protective Ointment

Net wt. 2.47 oz (70 g)

Made in India for:

Smith & Nephew Medical Ltd,

101 Hessle Road, Hull, HU3 2BN, England

Trademark of Smith & Nephew. Certain marks Reg'd U.S. Pat. & Tm. Off.

PACKAGE LABEL - PRINCIPAL DISPLAY PANEL - SECURA PROTECTIVE OINTMENT (159g)

#59431600

NDC-69740-316-00

Protective Ointment

Skin Protectant

For treatment and prevention of incontinence-associated dermatitis
Enriched with Vitamins A, D & E
Pediatric tested
CHG compatible
Enriched with Clove Oil

Smith&Nephew
Secura
Protective Ointment

Net wt. 5.6 oz (159 g)

Made in India for:
Smith & Nephew Medical Ltd,

101 Hessle Road, Hull, HU3 2BN, England
Trademark of Smith & Nephew. Certain marks Reg'd U.S. Pat. & Tm. Off.